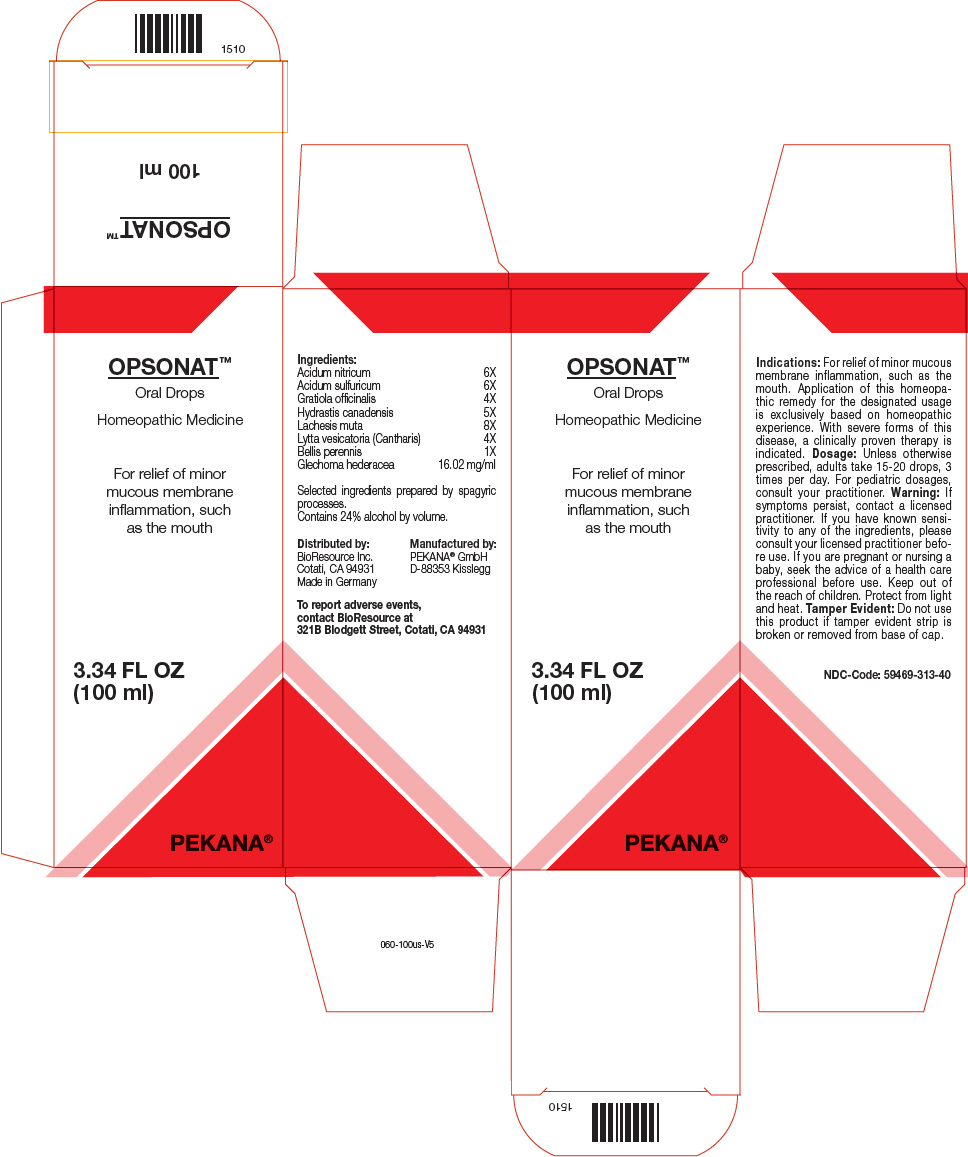 DRUG LABEL: OPSONAT
NDC: 59469-313 | Form: SOLUTION/ DROPS
Manufacturer: PEKANA Naturheilmittel GmbH
Category: homeopathic | Type: HUMAN OTC DRUG LABEL
Date: 20230111

ACTIVE INGREDIENTS: SILVER NITRATE 6 [hp_X]/100 mL; SULFURIC ACID 6 [hp_X]/100 mL; BELLIS PERENNIS WHOLE 1 [hp_X]/100 mL; LYTTA VESICATORIA 4 [hp_X]/100 mL; GRATIOLA OFFICINALIS WHOLE 4 [hp_X]/100 mL; GOLDENSEAL 5 [hp_X]/100 mL; LACHESIS MUTA VENOM 8 [hp_X]/100 mL; GLECHOMA HEDERACEA FLOWERING TOP 1602 mg/100 mL
INACTIVE INGREDIENTS: WATER; ALCOHOL

OPSONAT™

ACTIVE INGREDIENT

Ingredients:
Acidum nitricum | 6X
Acidum sulfuricum | 6X
Gratiola officinalis | 4X
Hydrastis canadensis | 5X
Lachesis muta | 8X
Lytta vesicatoria (Cantharis) | 4X
Bellis perennis | 1X
Glechoma hederacea | 16.02 mg/ml

Selected ingredients prepared by spagyric processes.

INACTIVE INGREDIENT

Contains 24% alcohol by volume.

Indications

PURPOSE

For relief of minor mucous membrane inflammation, such as the mouth. Application of this homeopathic remedy for the designated usage is exclusively based on homeopathic experience. With severe forms of this disease, a clinically proven therapy is indicated.

Dosage

Unless otherwise prescribed, adults take 15-20 drops, 3 times per day. For pediatric dosages, consult your practitioner.

Warning

ASK DOCTOR

If symptoms persist, contact a licensed practitioner. If you have known sensitivity to any of the ingredients, please consult your licensed practitioner before use. If you are pregnant or nursing a baby, seek the advice of a health care professional before use.

Keep out of the reach of children.

STORAGE AND HANDLING

Protect from light and heat.

Tamper Evident

Do not use this product if tamper evident strip is broken or removed from base of cap.

QUESTIONS

To report adverse events, contact BioResource at 321B Blodgett Street, Cotati, CA 94931

Distributed by:
BioResource Inc.
Cotati, CA 94931

Manufactured by:
PEKANA® GmbH
D-88353 Kisslegg

PRINCIPAL DISPLAY PANEL - 100 ml Bottle Box

OPSONAT™

Oral Drops

Homeopathic Medicine

For relief of minor
mucous membrane
inflammation, such
as the mouth

3.34 FL OZ
(100 ml)

PEKANA®